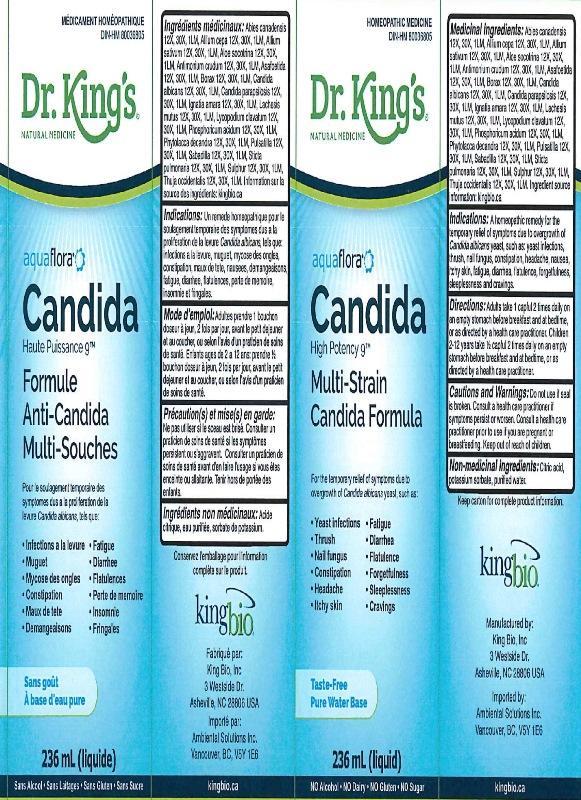 DRUG LABEL: Candida High Potency 9
NDC: 57955-1802 | Form: LIQUID
Manufacturer: King Bio Inc.
Category: homeopathic | Type: HUMAN OTC DRUG LABEL
Date: 20160504

ACTIVE INGREDIENTS: TSUGA CANADENSIS BARK 12 [hp_X]/236 mL; TSUGA CANADENSIS FLOWER BUD 12 [hp_X]/236 mL; ONION 12 [hp_X]/236 mL; GARLIC 12 [hp_X]/236 mL; ALOE 12 [hp_X]/236 mL; ANTIMONY TRISULFIDE 12 [hp_X]/236 mL; ASAFETIDA 12 [hp_X]/236 mL; SODIUM BORATE 12 [hp_X]/236 mL; CANDIDA ALBICANS 12 [hp_X]/236 mL; CANDIDA PARAPSILOSIS 12 [hp_X]/236 mL; STRYCHNOS IGNATII SEED 12 [hp_X]/236 mL; LACHESIS MUTA VENOM 12 [hp_X]/236 mL; LYCOPODIUM CLAVATUM SPORE 12 [hp_X]/236 mL; PHOSPHORIC ACID 12 [hp_X]/236 mL; PHYTOLACCA AMERICANA ROOT 12 [hp_X]/236 mL; PULSATILLA VULGARIS 12 [hp_X]/236 mL; SCHOENOCAULON OFFICINALE SEED 12 [hp_X]/236 mL; LOBARIA PULMONARIA 12 [hp_X]/236 mL; SULFUR 12 [hp_X]/236 mL; THUJA OCCIDENTALIS LEAFY TWIG 12 [hp_X]/236 mL
INACTIVE INGREDIENTS: ANHYDROUS CITRIC ACID; POTASSIUM SORBATE; WATER

Candida High Potency 9

ACTIVE INGREDIENT

Medicinal ingredients: Abies canadensis 12X, 30X, 1LM, Allium cepa 12X, 30X, 1LM, Allium sativum 12X, 30X, 1LM, Aloe socotrina 12X, 30X, 1LM, Antimonium crudum 12X, 30X, 1LM, Asafoetida 12X, 30X, 1LM, Borax 12X, 30X, 1LM, Candida albicans 12X, 30X, 1LM, Candida parapsilosis 12X, 30X, 1LM, Ignatia amara 12X, 30X, 1LM, Lachesis mutus 12X, 30X, 1LM, Lycopodium clavatum 12X, 30X, 1LM, Phosphoricum acidum 12X, 30X, 1LM, Phytolacca decandra 12X, 30X, 1LM, Pulsatilla 12X, 30X, 1LM, Sabadilla 12X, 30X, 1LM, Sticta pulmonaria 12X, 30X, 1LM, Sulphur 12X, 30X, 1LM, Thuja occidentalis 12X, 30X, 1LM. Ingredient source information: canada.kingbio.com Information sur la source des ingrédients: kingbio.ca

INACTIVE INGREDIENT

Non-medicinal ingredients: Citric acid, potassium sorbate, purified water.

Ingrédients non médicinaux: Acide citrique, eau purifiée, sorbate de potassium.

PURPOSE

Indications: A homeopathic remedy for the temporary relief of symptoms due to overgrowth of Candida albicans yeast, such as: yeast infections, thrush, nail fungus, constipation, headache, nausea, itchy skin, fatigue, diarrhea, flatulence, forgetfulness, sleeplessness and cravings.

Indications: un remede homeopathique pour le soulagement temporaire des symptomes dus a la proliferation de la levure Candida albicans, tels que: infections a la levure, muguet, mycose des ongles, constipation, maux de tete, nausees, demangeaisons, fatigue, diarrhee, flatulences, perte de memoire, insomnie et fringales.

DOSAGE AND ADMINISTRATION

Directions: Adults take 1 capful 2 times daily on an empty stomach before breakfast and at bedtime, or as directed by a health care practitioner. Children 2-12 years take ½ capful 2 times daily on an empty stomach before breakfast and a bedtime, or as directed by a health care practitioner.

Mode d'emploi: Adultes prendre 1 bouchon doseur à jeun, 2 fois par jour, avant le petit dejeuner et au coucher, ou selon l'avis d'un praticien de soins de santé. Enfants ages de 2 a 12 ans: prendre ½ bouchon doseur à jeun, 2 fois par jour, avant le petit dejeuner et au coucher, ou selon l'avis d'un praticien de soins de santé.

INDICATIONS AND USAGE

Indications: A homeopathic remedy for the temporary relief of symptoms due to overgrowth of Candida albicans yeast, such as:

- yeast infections
- thrush
- nail fungus
- constipation
- headache
- nausea
- itchy skin
- fatigue
- diarrhea
- flatulence
- forgetfulness
- sleeplessness
- cravings

Indications: Un remede homeopathique pour le soulagement temporaire des symptomes dus a la proliferation de la levure Candida albicans, tels que:

- infections a la levure
- muguet
- mycose des ongles
- constipation
- maux de tete
- nausees
- demangeaisons
- fatigue
- dearrhee
- flatulences
- perte de memoire
- insomnie et fringales

WARNINGS

Cautions and Warnings: Do not use if seal is broken. Consult a health care practitioner if symptoms persist or worsen. Consult a health care practitioner prior to use if you are pregnant or breastfeeding.

Précaution(s) et mise(s) en garde: Na pas utiliser si le sceau est brise. Consulter un praticien de soins de santé si les symptômes persistent ou s'aggravent. Consulter un praticien de soins de santé avant d'en faire l'usage si vous êtes enceinte ou allaitante.

Keep out of reach of chi